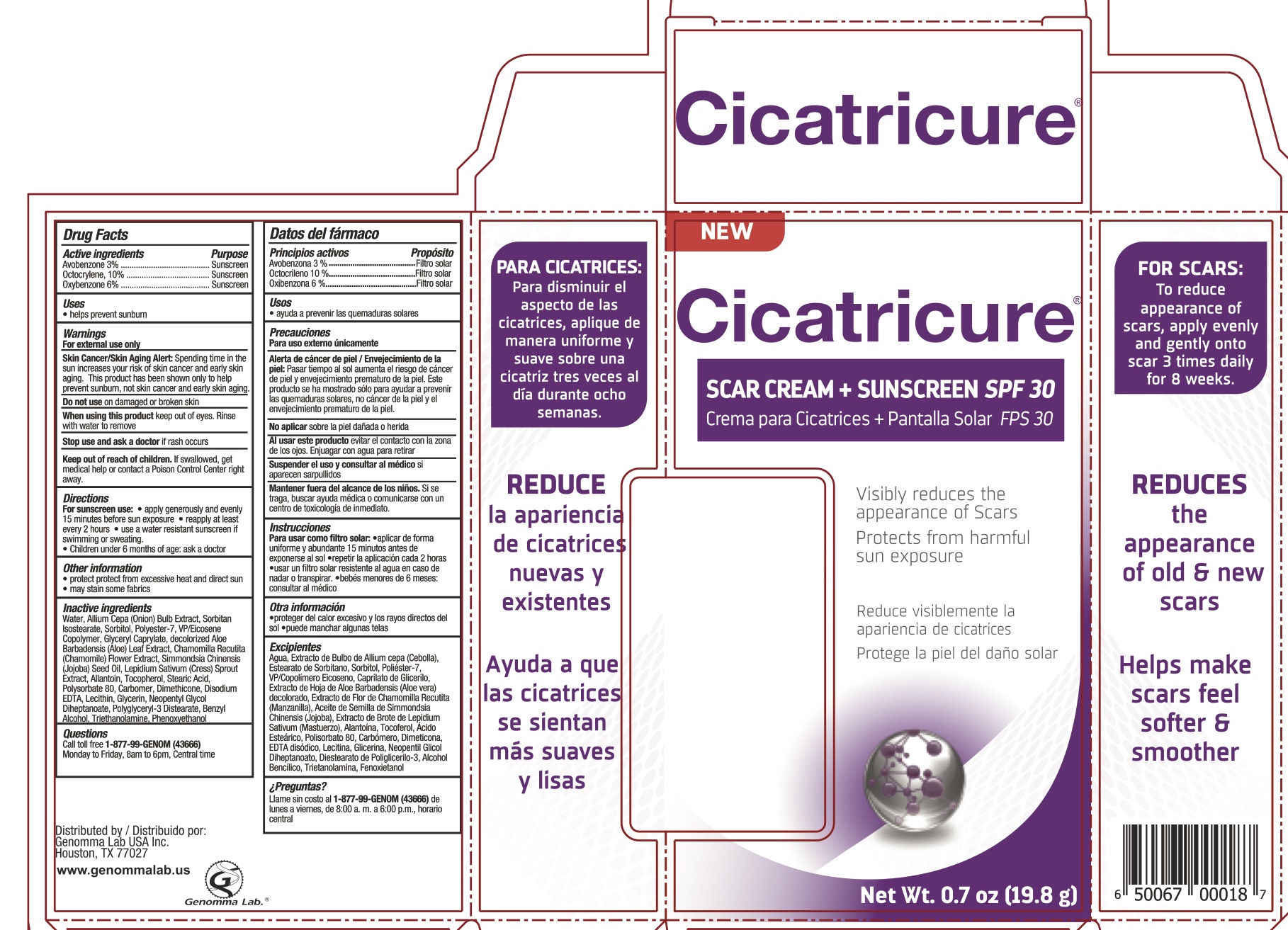 DRUG LABEL: Scar Cream SPF 30
NDC: 50066-119 | Form: CREAM
Manufacturer: Genomma Lab
Category: otc | Type: HUMAN OTC DRUG LABEL
Date: 20190222

ACTIVE INGREDIENTS: AVOBENZONE 3 g/100 g; OXYBENZONE 6 g/100 g; OCTOCRYLENE 10 g/100 g
INACTIVE INGREDIENTS: STEARIC ACID; GARDEN CRESS SPROUT; GLYCERIN; NEOPENTYL GLYCOL DIHEPTANOATE; POLYGLYCERYL-3 DISTEARATE; POLYSORBATE 80; TROLAMINE; JOJOBA OIL; BENZYL ALCOHOL; EDETATE DISODIUM; CARBOXYPOLYMETHYLENE; MATRICARIA RECUTITA LEAF; PHENOXYETHANOL; DIMETHICONE 200; ALOE VERA LEAF; GLYCERYL CAPRYLATE; VINYLPYRROLIDONE/EICOSENE COPOLYMER; WATER; ONION; SORBITOL; POLYESTER-7; SORBITAN ISOSTEARATE; LECITHIN, SOYBEAN; ALLANTOIN; .ALPHA.-TOCOPHEROL

Active Ingredients

Avobenzone 3%, Octocrylene 10%, Oxybenzone 6%

Purpose

Sunscreen

Uses

- Helps prevent sunburn

Warnings

For external use only.

Skin Cancer/Skin Aging Alert: spending time in the sun increases your risk of skin cancer and early skin aging. This product has been shown only to help prevent sunburn, not skin cancer and early skin aging.

Do not use on damaged or broken skin. When using this product keep out of eyes. Rinse eyes with water to remove.

Stop use and ask a doctor if rash occurs.

Keep Out of Reach of Children.

If swallowed, get medical help or contact a Poison Control Center right away.

Directions

Apply generously and evenly 15 minutes before sun exposure. Reapply:

- at least every 2 hours
- use a water resistant sunscreen if swimming or sweating

Children under 6 months: ask a doctor.

Inactive Ingredients

Water, Allium Cepa (Onion) Bulb Extract, Sorbitan Isostearate, Sorbitol, Polyester-7, VP/Eicosene Copolymer, Glyceryl Caprylate, decolorized Aloe Barbadensis Leaf Extract, Chamomilla Recutita Flower Extract, Simmondsia Chinensis (Jojoba) Seed Oil, Lepidium Sativum (Cress) Sprout Extract, Allantoin, Tocopherol, Stearic Acid, Polysorbate 80, Carbomer, Dimethicone, Disodium EDTA, Lecithin, Glycerin, Neopentyl Glycol Diheptanoate, Polyglyceryl-3 Distearate, Benzyl Alcohol, Triethanolamine, Phenoxyethanol